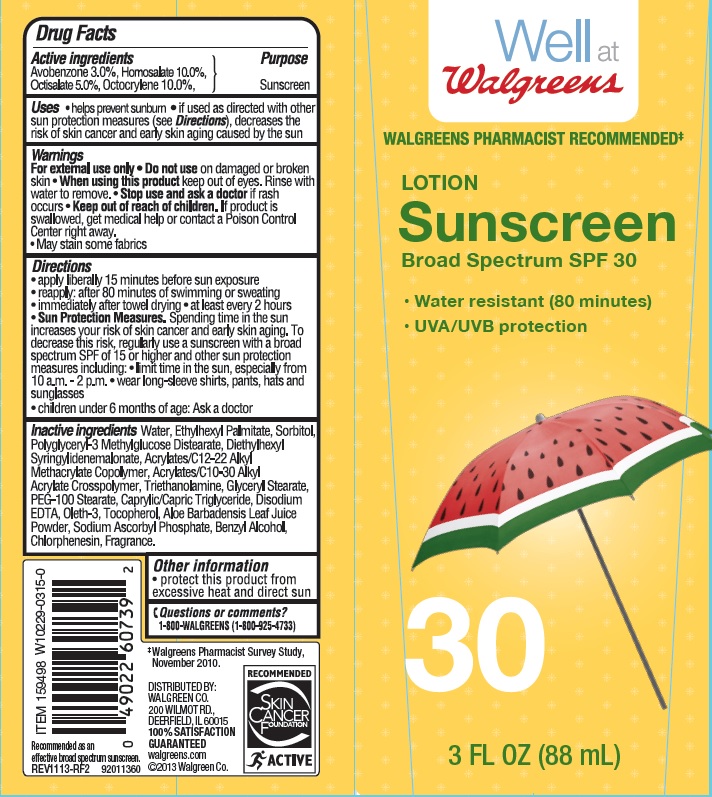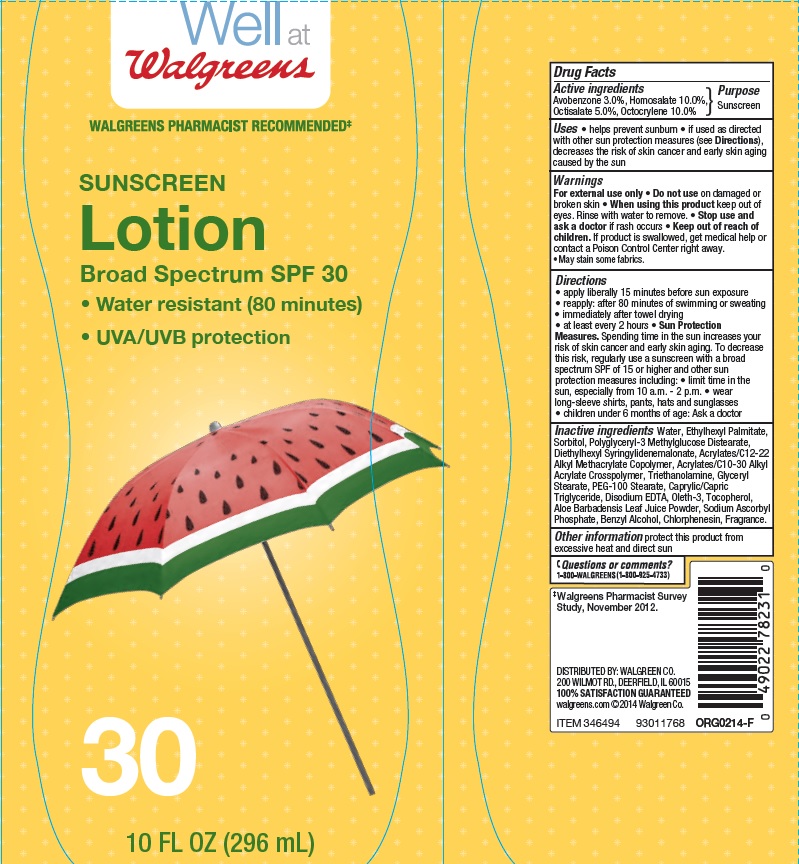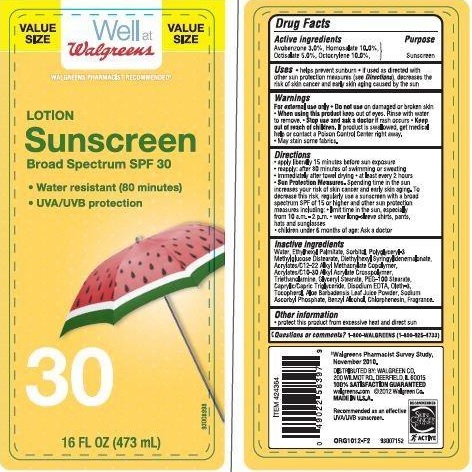 DRUG LABEL: Walgreens Sunscreen
NDC: 0363-4016 | Form: LOTION
Manufacturer: WALGREEN CO.
Category: otc | Type: HUMAN OTC DRUG LABEL
Date: 20160609

ACTIVE INGREDIENTS: AVOBENZONE 3 g/100 g; HOMOSALATE 10 g/100 g; OCTISALATE 5 g/100 g; OCTOCRYLENE 10 g/100 g
INACTIVE INGREDIENTS: WATER; ETHYLHEXYL PALMITATE; SORBITOL; DIETHYLHEXYL SYRINGYLIDENEMALONATE; TROLAMINE; GLYCERYL MONOSTEARATE ; PEG-100 STEARATE; TOCOPHEROL; EDETATE DISODIUM; OLETH-3; ALOE VERA LEAF; SODIUM ASCORBYL PHOSPHATE; BENZYL ALCOHOL; CHLORPHENESIN

Drug Facts

Active Ingredients

Avobenzone 3.0 %

Homosalate 10.0%

Octisalate 5.0%

Octocrylene 10.0%

Purpose

Sunscreen

Uses

- helps prevent sunburn
- if used as directed with other sun protection measures (see Directions) decrease the risk of skin cancer and early skin aging caused by the sun

Warnings

For External use only

Do not use

on damaged or broken skin

When using this product

keep out of eyes. Rinse with water to remove

Stop use and ask a doctor

If rash occurs

Keep out of reach of children

If product is swallowed get medical help or contact a Poison Control Center right away.

- May stain some fabrics.

Directions

- apply liberally 15 minutes before sun exposure
- reapply: after 80 minutes of swimming or sweating
- immediately after towel drying
- at least every 2 hours

Sun protection measures.

Spending time in the sun increase your risk of skin cancer and early skin aging. To decrease this risk regularly use a sunscreen with a broad spectrum SPF of 15 or higher and other sun protection measures including:

- Limit time in the sun, especially from 10 am - 2 pm
- Wear long sleeves shirts, pants, hats and sunglasses
- children under 6 month of age: Ask a doctor

Inactive Ingredients

Water, Ethylhexyl Palmitate, Sorbitol, Polyglyceryl-3 Methylglucose Distearate, Diethylhexyl Syringylidenemalonate, Acrylates/C12-22 Alkyl Methacrylate Copolymer, Acrylates/C10-30 Alkyl Acrylate Crosspolymer, Triethanolamine, Glyceryl Stearate, PEG-100 Stearate, Caprylic/ Capric Triglyceride, Disodium EDTA, Oleth-3, Tocopherol, Aloe Barbadensis Leaf Juice Powder, Sodium Ascorbyl Phosphate, Benzyl Alcohol, Chlorphenesin, Fragrance.

Other information

Protect this product from excessive heat and direct sun.

Questions or comments

1-800-WALGREENS (1-800-925-4733)

Principal Display Panel

NDC 0363-4016-29

VALUE SIZE

Well at

Walgreens

LOTION

Sunscreen

Broad Spectrum SPF 30

- Water resistant (80 minutes)
- UVA/UVB protection

16 FL OZ (473 mL)

NDC 0363-4016-22

Well at Walgreens

WALGREENS PHARMACIST RECOMMENDED

SUNSCREEN

Lotion

Broad Spectrum SPF 30

- Water resistant (80 minutes)
- UVA/UVB protection

30

10 FL OZ (296 mL)

NDC 0363-4016-19

Well at Walgreens

WALGREENS PHARMACIST RECOMMENDED

SUNSCREEN

Lotion

Broad Spectrum SPF 30

- Water resistant (80 minutes)
- UVA/UVB protection

30

3 FL OZ (88 mL)